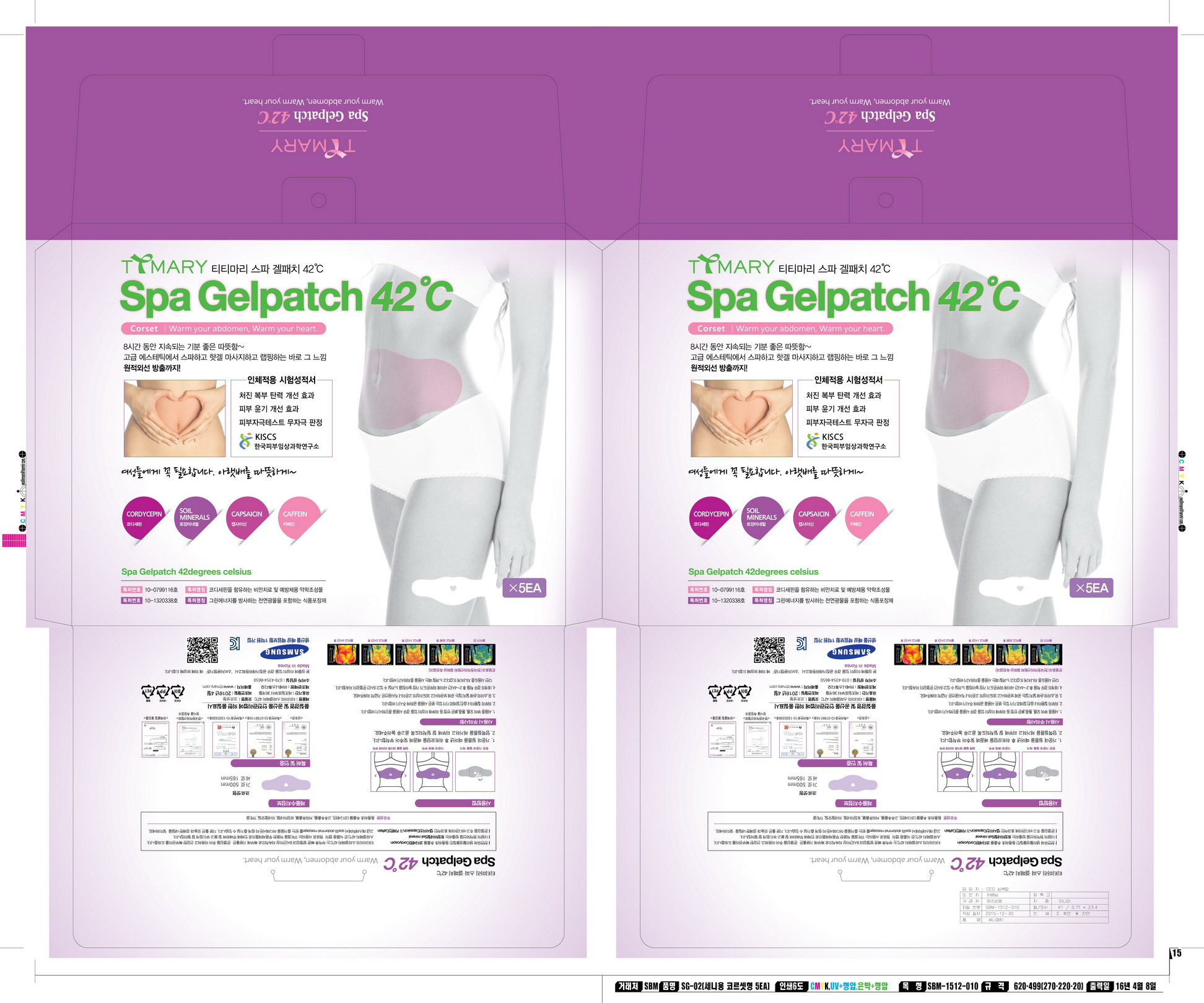 DRUG LABEL: SpaGelpatch 42degrees celsius CORSET
NDC: 71829-0002 | Form: PATCH
Manufacturer: SENNY STUDIO Co., Ltd
Category: otc | Type: HUMAN OTC DRUG LABEL
Date: 20171120

ACTIVE INGREDIENTS: CAPSICUM ANNUUM WHOLE 0.05 g/100 g
INACTIVE INGREDIENTS: CORDYCEPIN

Drug Facts

ACTIVE INGREDIENT

Capsicum annuum extract

INACTIVE INGREDIENT

Hydrogenated Dicyclopentadiene/Isopentene/Isoprene/Styrene Copolymer (and) Mineral Oil (and) Hydrogenated Styrene/Butadiene Copolymer, coffee seed extract, soil mineral, cordycepin

PURPOSE

Improvement of stomach abdomen elasticity
Skin gloss improvement effect

keep out of reach of the children

INDICATIONS AND USAGE

Remove both films and attach to the abdomen and rub well

WARNINGS

Cautions :

1. When you use this product and find any of following problems, stop using it. if you keep using it despite the problem, the symptom will get worse, so you will have to go see a dermatologist.

- During use, if you have red spots, swelling, itching, or any other stimuli.

- if the applied region has any problem above for direct light.

2. Do not use the product on wound or dermatitis. 3.Attentive points for storage and treatment :

- Store it in the place where infants or children cannot touch

- do not store it where it has either high or low temperature or there is direct light.

DOSAGE AND ADMINISTRATION

for external use only